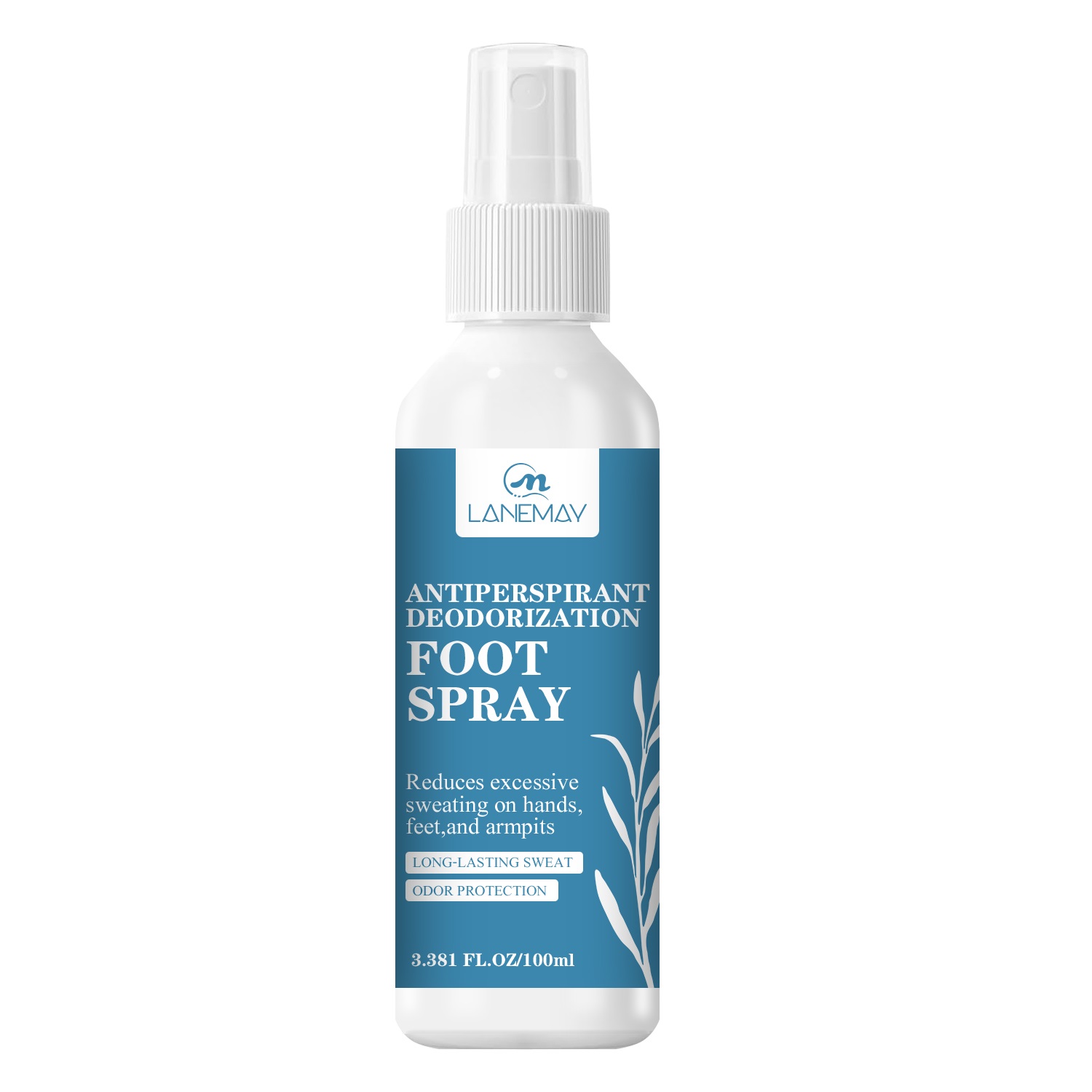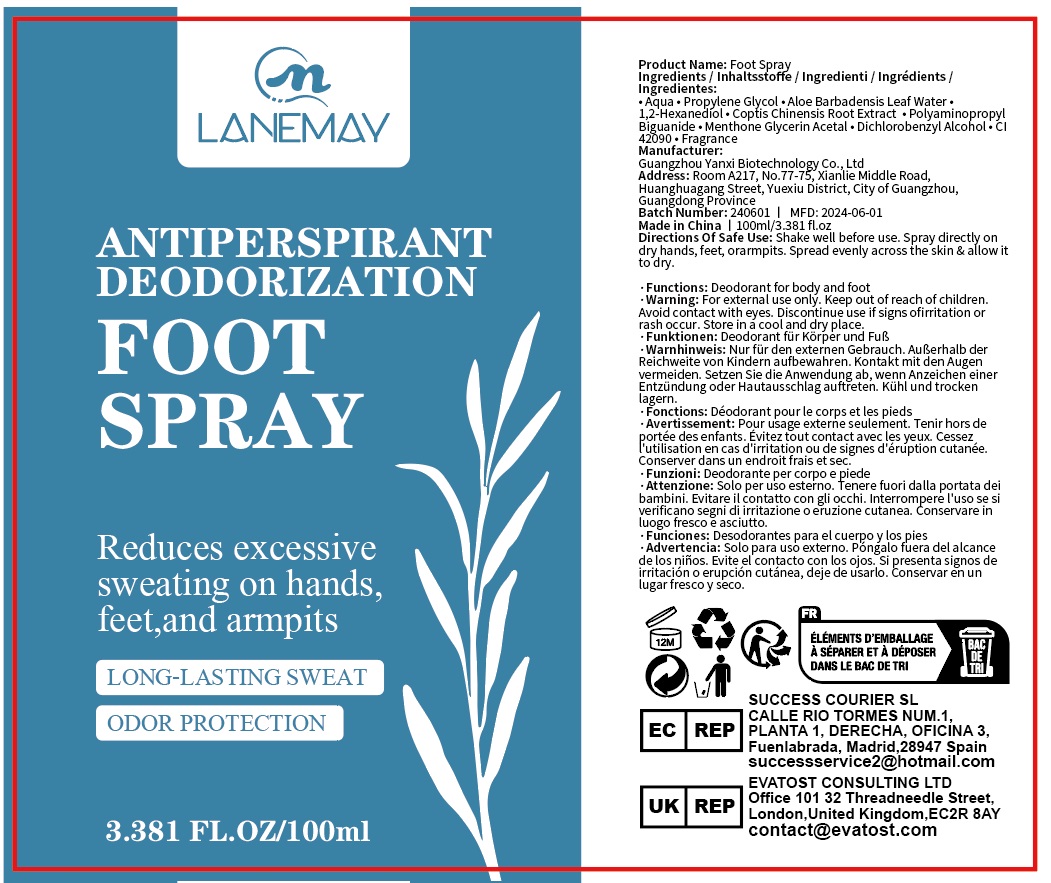 DRUG LABEL: Antiperspirant Deodorization
NDC: 84025-057 | Form: SPRAY
Manufacturer: Guangzhou Yanxi Biotechnology Co., Ltd
Category: otc | Type: HUMAN OTC DRUG LABEL
Date: 20240710

ACTIVE INGREDIENTS: POLYAMINOPROPYL BIGUANIDE 2 mg/100 mL; 1,2-HEXANEDIOL 3 mg/100 mL
INACTIVE INGREDIENTS: WATER

DOSAGE AND ADMINISTRATION

Use as a foot spray

WARNINGS

Keep out of children

INACTIVE INGREDIENT

Aqua

INDICATIONS AND USAGE

Reduces excessivesweating on hands, feet and armpits

Keep out of children

PURPOSE

long-lasting sweat

odor protection